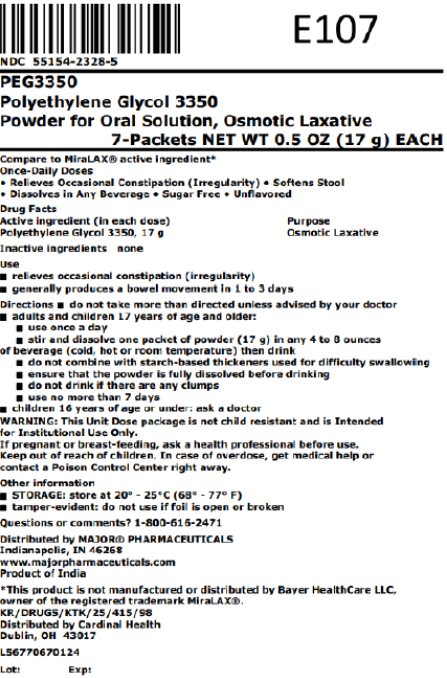 DRUG LABEL: Polyethylene glycol 3350
NDC: 55154-2328 | Form: POWDER, FOR SOLUTION
Manufacturer: Cardinal Health 107, LLC
Category: otc | Type: HUMAN OTC DRUG LABEL
Date: 20251023

ACTIVE INGREDIENTS: POLYETHYLENE GLYCOL 3350 17 g/17 g

Major 44-726

Active ingredient (in each dose)

Polyethylene Glycol 3350, 17 g

Purpose

Osmotic Laxative

Use

- relieves occasional constipation (irregularity)
- generally produces a bowel movement in 1 to 3 days

Warnings

Allergy alert: Do not use if you are allergic to polyethylene glycol

Do not use

if you have kidney disease, except under the advice and supervision of a doctor

Ask a doctor before use if you have

- nausea, vomiting or abdominal pain
- a sudden change in bowel habits that lasts over 2 weeks
- irritable bowel syndrome

Ask a doctor or pharmacist before use if you are

taking a prescription drug

When using this product

you may have loose, watery, more frequent stools

Stop use and ask a doctor if

- you get diarrhea
- you need to use a laxative for longer than 1 week
- you have rectal bleeding or your nausea, bloating, cramping or abdominal pain gets worse. These may be signs of a serious condition.

If pregnant or breast-feeding,

ask a health professional before use.

Keep out of reach of children.

In case of overdose, get medical help or contact a Poison Control Center right away.

Directions

- do not take more than directed unless advised by your doctor
- adults and children 17 years of age and older:
  - use once a day
  - stir and dissolve one packet of powder (17 g) in any 4 to 8 ounces of beverage (cold, hot or room temperature) then drink
  - do not combine with starch-based thickeners used for difficulty swallowing
  - ensure that the powder is fully dissolved before drinking
  - do not drink if there are any clumps
  - do not use more than 7 days
- children 16 years of age or under: ask a doctor

Other information

- store at 20° - 25°C (68° - 77°F)
- tamper-evident: do not use if foil is open or broken

Inactive ingredients

none

Questions or comments?

1-800-616-2471

.

Overbagged with 7 x 0.5 oz (17g g) Net Wt packets in each bag, NDC 55154-2328-5

WARNING: This Unit Dose package is not child resistant and is Intended for Institutional Use Only. Keep this and all drugs out of the reach of children.

Rev. 03/22 | M-17 | Re-Order No. 701066

Distributed By:

Cardinal Health

Dublin, OH 43017

L56770670124

Principal Display Panel

NDC 55154-2328-5

PEG3350

Polyethylene Glycol 3350

Powder for Oral Solution, Osmotic Laxative

7-Packets NET WT 0.5 OZ (17 g) EACH